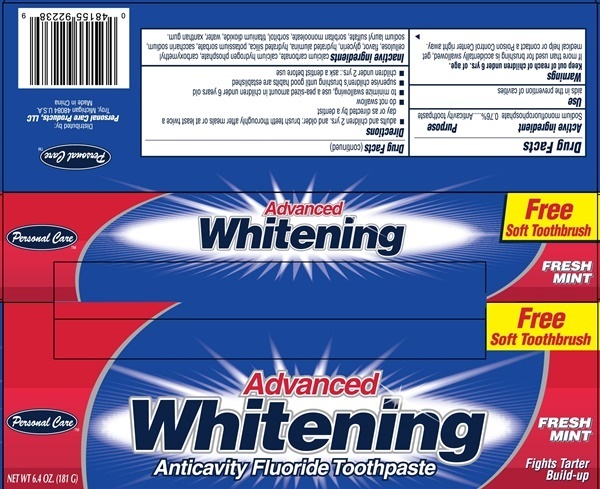 DRUG LABEL: Advanced Whitening Anticavity Fluoride
NDC: 29500-9223 | Form: PASTE, DENTIFRICE
Manufacturer: Personal Care Products, LLC
Category: otc | Type: HUMAN OTC DRUG LABEL
Date: 20170719

ACTIVE INGREDIENTS: SODIUM MONOFLUOROPHOSPHATE 1000 mg/181 g
INACTIVE INGREDIENTS: CALCIUM CARBONATE; ANHYDROUS DIBASIC CALCIUM PHOSPHATE; POWDERED CELLULOSE; GLYCERIN; ALUMINUM OXIDE; HYDRATED SILICA; POTASSIUM SORBATE; SACCHARIN SODIUM; SODIUM LAURYL SULFATE; SORBITAN MONOOLEATE; SORBITOL; TITANIUM DIOXIDE; WATER; XANTHAN GUM

ADVANCED WHITENING ANTICAVITY FLUORIDE - 9223

Drug Facts Active ingredient

Sodium Monofluorophosphate 0.76%

Purpose

Anticavity toothpaste

Uses

aids in the prevention of cavities

Warnings

If more than used for brushing is accidentally swallowed get medical help or contact a Poison Control Center right away.

Keep out of reach of children under 6 yrs of age.

Directions

- adults and children 2 years. and older: brush teeth thoroughly after meals or at least twice a day or as directed by a dentist.
- do not swallow
- to minimize swallowing, use a pea-sized amount in children under 6 years old
- supervise children's brushing until good habits are established
- children under 2 yrs: ask a dentist before use.

Inactive ingredients

calcium carbonate, calcium hydrogen phosphate, carboxymethyl cellulose, flavor, glycerin, hydrated alumina, hydrated silica, potassium sorbate, saccharin sodium, sodium lauryl sulfate, sorbitan monooleate, sorbitol, titanium dioxide, water, xanthan gum.

Advanced Whitening Anticavity product label

Personal Care™

Advanced Whitening Anitcavity Fluoride Toothpaste

FRESH MINT

Fights Tarter Build-up

NET WT 6.4 OZ. (181 G)

Free Soft Toothrush

Distributed by:
Personal Care Products, LLC
Troy, Michigan 48084 U.S.A.
Made in China